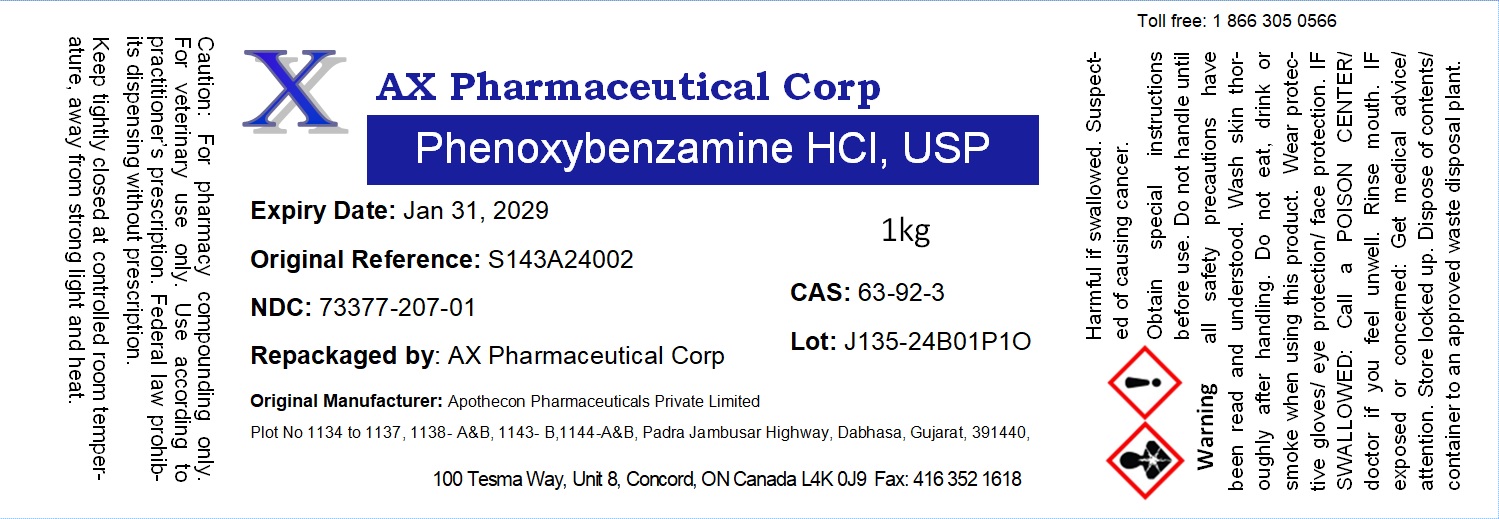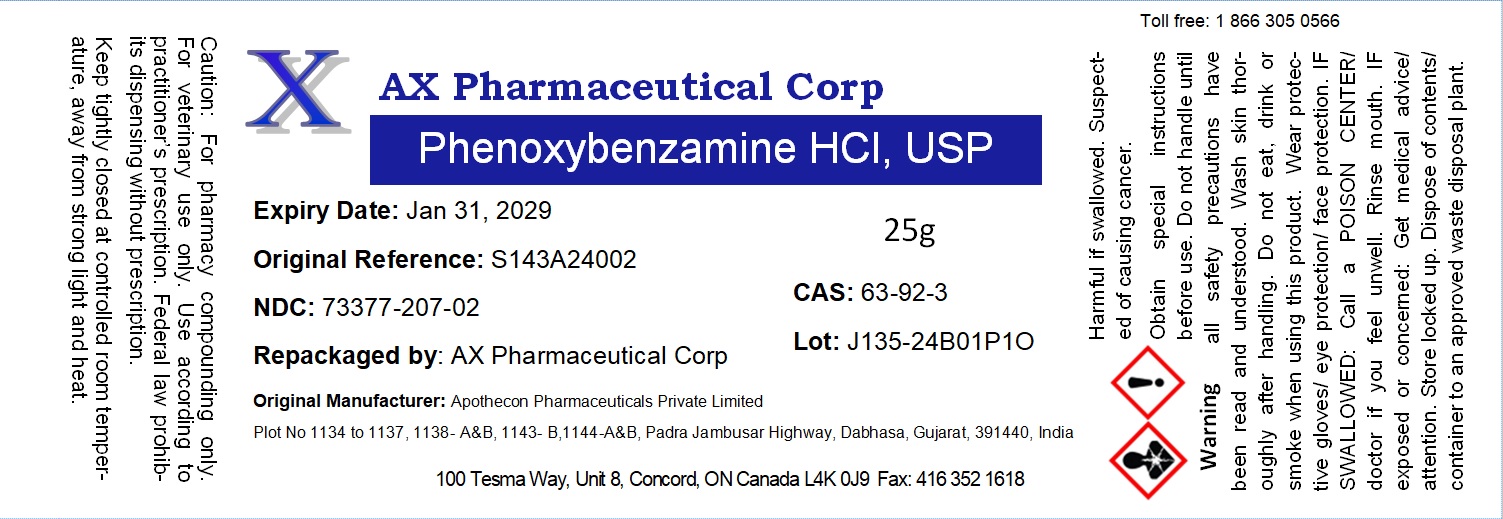 DRUG LABEL: Phenoxybenzamine HCl
NDC: 73377-207 | Form: POWDER
Manufacturer: AX Pharmaceutical Corp.
Category: other | Type: BULK INGREDIENT - ANIMAL DRUG
Date: 20250212

ACTIVE INGREDIENTS: PHENOXYBENZAMINE HYDROCHLORIDE 1 g/1 g

Phenoxybenzamine HCl